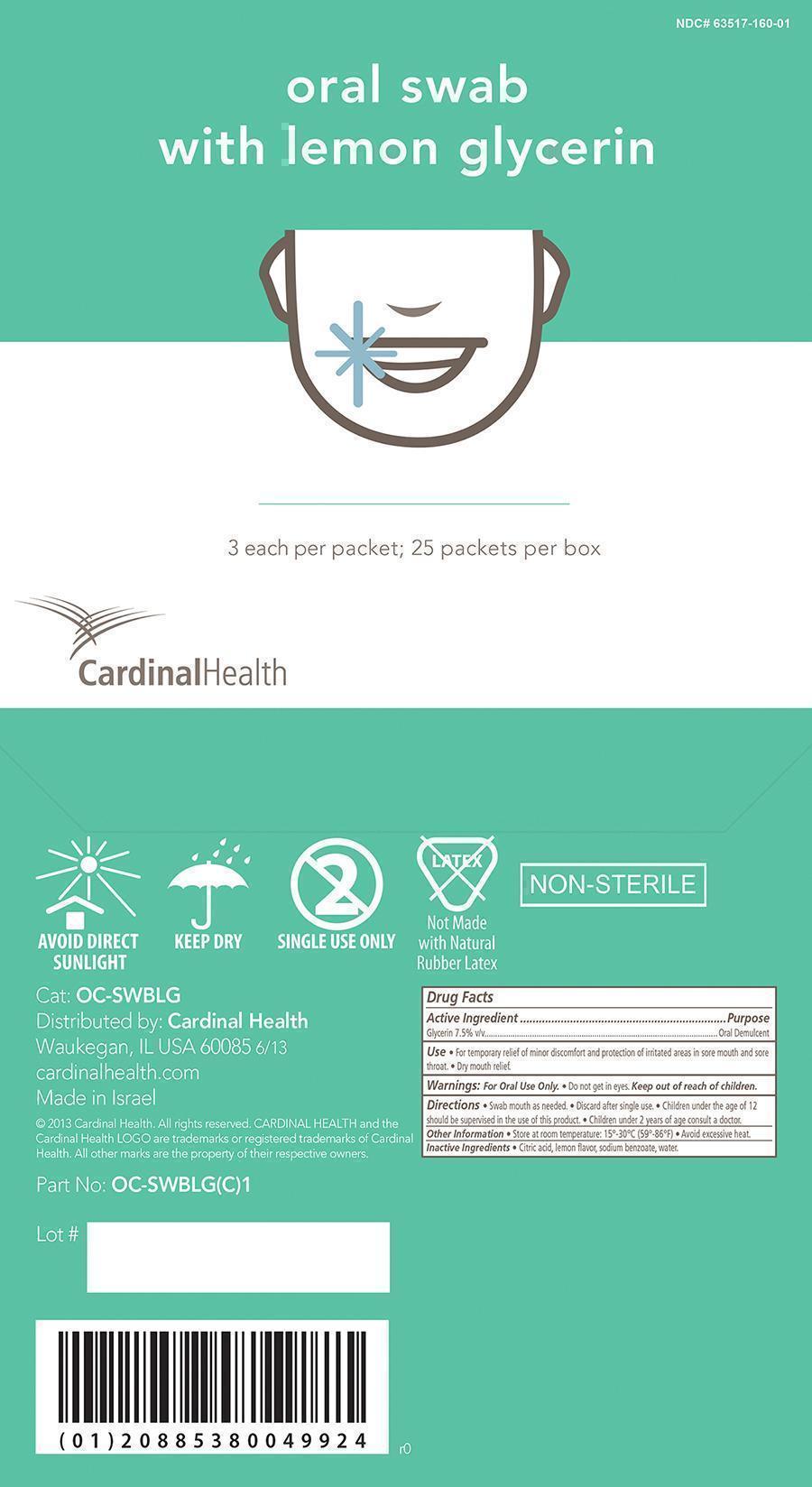 DRUG LABEL: Lemon Glycerin
NDC: 63517-160 | Form: SWAB
Manufacturer: Cardinal Health
Category: otc | Type: HUMAN OTC DRUG LABEL
Date: 20131218

ACTIVE INGREDIENTS: GLYCERIN 7.5 g/100 g
INACTIVE INGREDIENTS: SODIUM BENZOATE; CITRIC ACID MONOHYDRATE; WATER

Lemon Glycerin Swabsticks

Active Ingredient

Active Ingredient Purpose

Glycerin 7.5% v/v Oral Demulcent

Purpose

For temporary relief of minor discomfort and protection of irritated areas in sore mouth and sore throat.

Warnings

Warning:

For Oral Use Only.

- Do not get in eyes.

KEEP OUT OF REACH OF CHILDREN

Indications and Usage

- For temporary relief of minor soreness and/or irritation of the mouth.
- Dry mouth relief.

Dosage and Administration

Administration

- Swab mouth as needed.
- Discard after single use.

Dosage

- Children under the age of 12 should be supervised in the use of this product.
- Children under 2 years of age consult a doctor.

Other information

- Store at room temperature. 15 deg - 30 deg C, 58 deg - 86 deg F
- Avoid excessive heat.

Inactive ingredients:

Inactive ingredients: Citric acid, lemon flavor, sodium benzoate, water

Principal Display Panel

Cardinal Lemon Swab.jpg